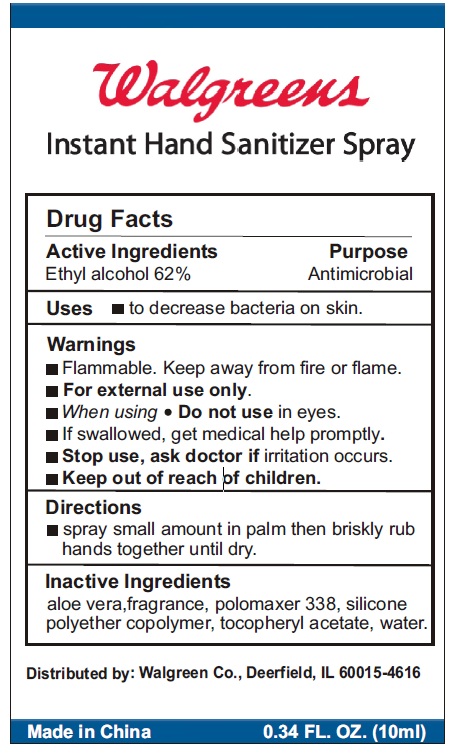 DRUG LABEL: WALGREENS INSTANT HAND SANITIZER
NDC: 0363-9320 | Form: SPRAY
Manufacturer: WALGREEN CO
Category: otc | Type: HUMAN OTC DRUG LABEL
Date: 20101011

ACTIVE INGREDIENTS: ALCOHOL 62 mL/100 mL
INACTIVE INGREDIENTS: ALOE; WATER

WALGREENS INSTANT HAND SANITIZER SPRAY 10ML

Drug Facts

Active Ingredients Purpose

Ethyl Alcohol 62% Antimicrobial

Purpose

Antimicrobial

Uses

To decrease bacteria on the skin.

Warnings

Flammable. keep away from fire or flame

For external use only.

When using do not use in eyes

If swallowed, get medical help promptly

Stop use, ask doctor if irritation occurs.

Keep out of reach of children

Directions

Spray small amount in palm then briskly rub hands together until dry.

Inactive Ingredients

Aloe vera, fragrance, polomaxer 338, silicone polyether copolymer, tocopheryl acetate, water

DESCRIPTION

WALGREENS INSTANT HAND SANITIZER SPRAY

Distributed by: Walgreen Co., Deerfield, IL 60015-4616

Made in China
0.34 fl oz (10 ml)